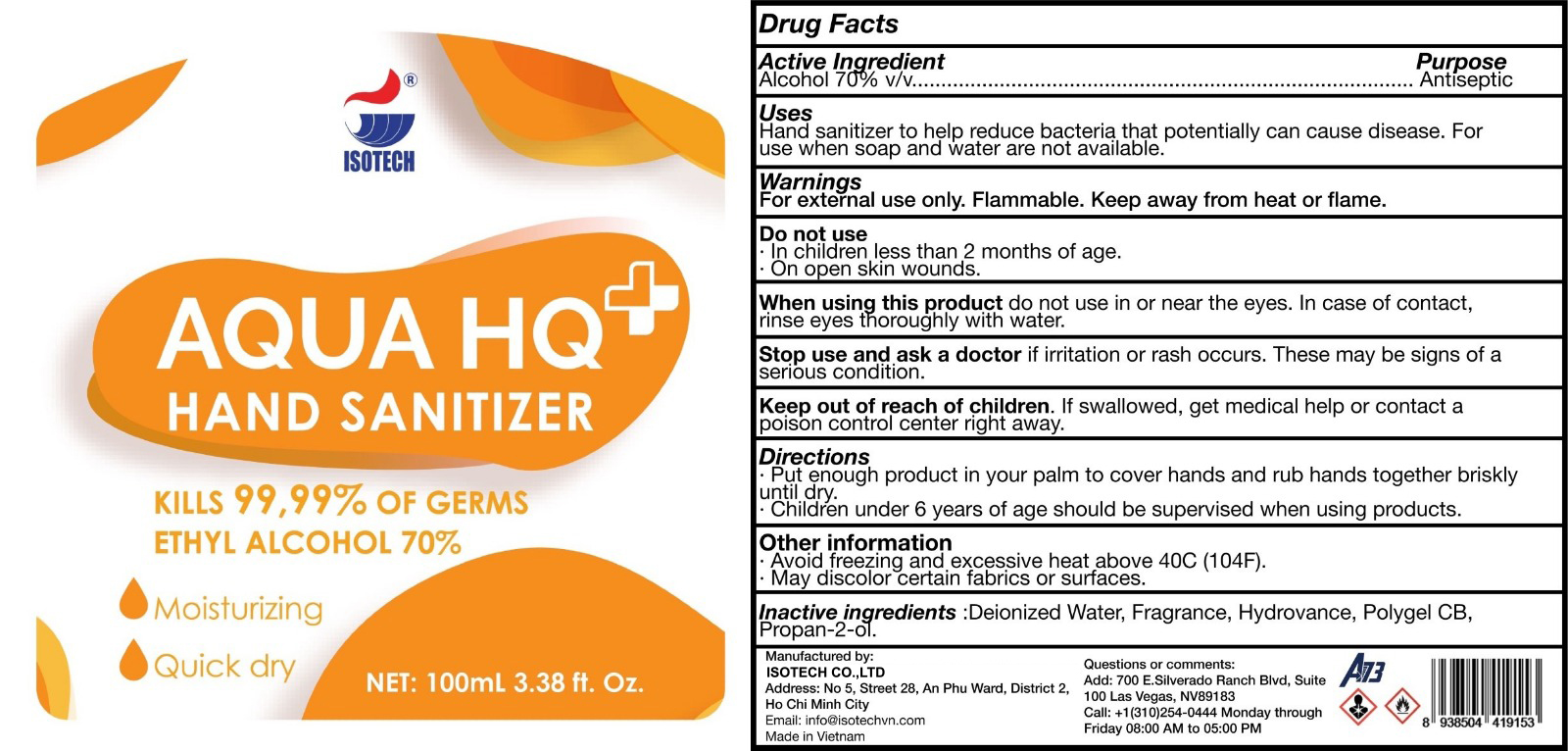 DRUG LABEL: AQUA HQ
NDC: 81177-111 | Form: GEL
Manufacturer: ISOTECH CO.,LTD
Category: otc | Type: HUMAN OTC DRUG LABEL
Date: 20210129

ACTIVE INGREDIENTS: ALCOHOL 70 mL/100 mL
INACTIVE INGREDIENTS: CARBOMER 940; ISOPROPYL ALCOHOL; ALOE VERA LEAF; HYDROXYETHYL UREA; WATER

AQUAHQ Sanitizer Orange Label 100mL

Active Ingredient(s)

Alcohol 70% v/v. Purpose: Antiseptic

Purpose

Antiseptic, Hand Sanitizer

Use

Hand Sanitizer to help reduce bacteria that potentially can cause disease. For use when soap and water are not available.

Warnings

For external use only. Flammable. Keep away from heat or flame

Do not use

- in children less than 2 months of age
- on open skin wounds

When using this product keep out of eyes, ears, and mouth. In case of contact with eyes, rinse eyes thoroughly with water.
Stop use and ask a doctor if irritation or rash occurs. These may be signs of a serious condition.
Keep out of reach of children. If swallowed, get medical help or contact a Poison Control Center right away.

Stop use and ask a doctor if irritation or rash occurs. These may be signs of a serious condition.

Keep out of reach of children. If swallowed, get medical help or contact a Poison Control Center right away.

Directions

Put enough product in your palm to cover hands and rub hands together briskly until dry.

Children under 6 years of age should be supervised when using products.

Other information

Avoid freezing and excessive heat above 40C (104F)

May discolor certain fabrics or surfaces

Inactive ingredients

Deionized water, Fragrance, Hyrovance, Polygel CB, Propan-2-ol

Package Label - Principal Display Panel

100 mL NDC: 81177-111-12